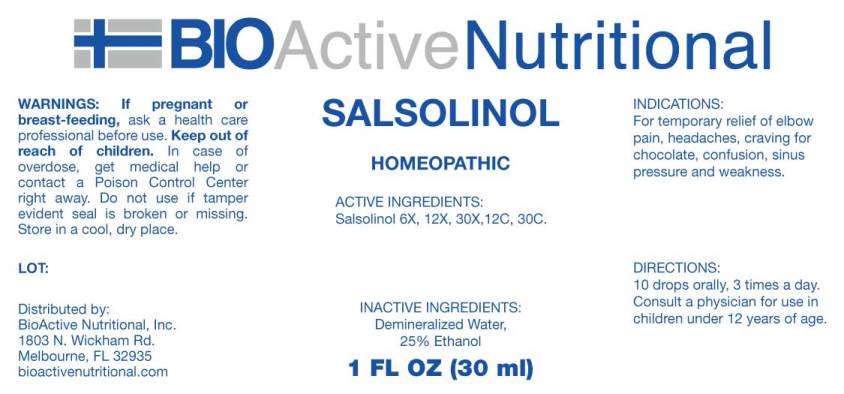 DRUG LABEL: Salsolinol
NDC: 43857-0501 | Form: LIQUID
Manufacturer: BioActive Nutritional, Inc.
Category: homeopathic | Type: HUMAN OTC DRUG LABEL
Date: 20181207

ACTIVE INGREDIENTS: SALSOLINOL HYDROCHLORIDE, (+/-)- 6 [hp_X]/1 mL
INACTIVE INGREDIENTS: WATER; ALCOHOL

Drug Facts:

ACTIVE INGREDIENTS:

Salsolinol (Hydrochloride) 6X, 12X, 30X, 12C, 30C.

INDICATIONS:

For temporary relief of elbow pain, headaches, craving for chocolate, confusion, sinus pressure and weakness.

WARNINGS:

If pregnant or breast-feeding, ask a health care professional before use.

Keep out of reach of children. In case of overdose, get medical help or contact a Poison Control Center right away.

Do not use if tamper evident seal is broken or missing.

Store in cool, dry place.

Keep out of reach of children. In case of overdose, get medical help or contact a Poison Control Center right away.

DIRECTIONS:

10 drops orally, 3 times a day. Consult a physician for use in children under 12 years of age.

INDICATIONS:

For temporary relief of elbow pain, headaches, craving for chocolate, confusion, sinus pressure and weakness.

INACTIVE INGREDIENTS:

Demineralized Water, 25% Ethanol.

QUESTIONS:

Distributed by:
BioActive Nutritional, Inc.
1803 N. Wickham Rd.
Melbourne, FL 32935
bioactivenutritional.com

PACKAGE LABEL DISPLAY:

BIOActive Nutritional
SALSOLINOL
HOMEOPATHIC
1 FL OZ (30 ml)